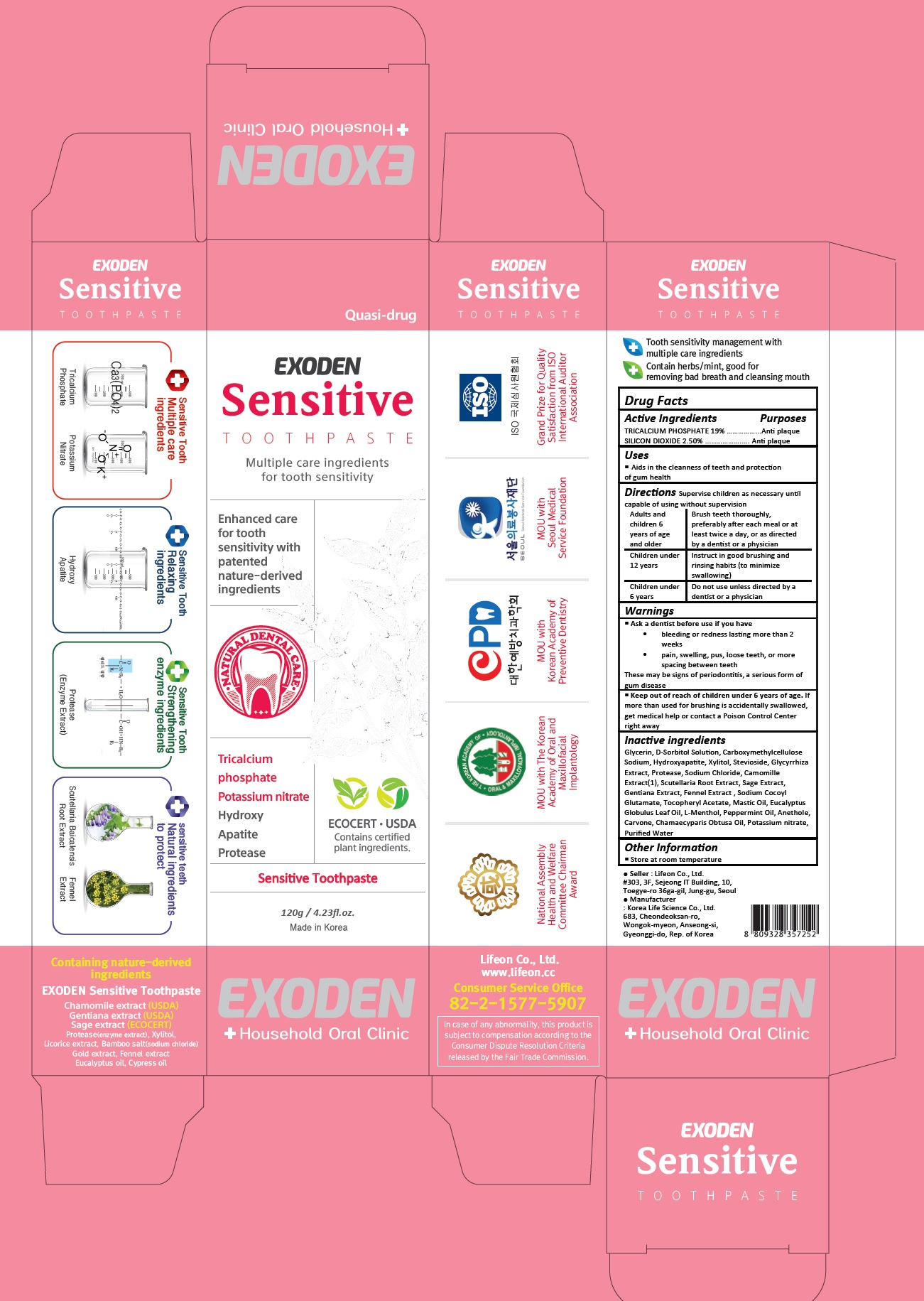 DRUG LABEL: Exoden Sensitive
NDC: 70602-006 | Form: PASTE
Manufacturer: LIFEON Corp.
Category: otc | Type: HUMAN OTC DRUG LABEL
Date: 20210311

ACTIVE INGREDIENTS: TRICALCIUM PHOSPHATE 19 g/100 g; SILICON DIOXIDE 2.5 g/100 g
INACTIVE INGREDIENTS: GLYCERIN; SORBITOL SOLUTION; CARBOXYMETHYLCELLULOSE SODIUM, UNSPECIFIED; TRIBASIC CALCIUM PHOSPHATE; XYLITOL; GLUCOSYL STEVIOL; LICORICE; SODIUM CHLORIDE; CHAMOMILE; SCUTELLARIA BAICALENSIS ROOT; CLARY SAGE; GENTIANA LUTEA ROOT; SODIUM COCOYL GLUTAMATE; .ALPHA.-TOCOPHEROL ACETATE; EUCALYPTUS OIL; LEVOMENTHOL; PEPPERMINT OIL; ANETHOLE; CARVONE, (+/-)-; CHAMAECYPARIS OBTUSA WOOD OIL; POTASSIUM NITRATE; WATER

70602-006_Exoden Sensitive Toothpaste

ACTIVE INGREDIENT

Tricalcium Phosphate 19%

Silicon dioxide 2.5%

PURPOSE

Anti plaque

INDICATIONS AND USAGE

Aids in cleanness of teeth and protection of gum health

DOSAGE AND ADMINISTRATION

Supervise children as necessary until capable of using without supervision

Adults and children 6 years of age and older: Brush teeth thoroughly, preferably after each meal or at least twice a day, or as directed by a dentist or a physician

Children under 12 years: Instruct in good brushing and rinsing habits (to minimize swallowing)

Children under 6 years: Do not use unless directed by a dentist or a physician

WARNINGS

Ask a dentist before use if you have
• bleeding or redness lasting more than 2 weeks
• pain, swelling, pus, loose teeth, or more spacing between teeth
These may be signs of periodontitis, a serious form of gum disease

Keep out of reach of children under 6 years of age. If more than used for brushing is accidentally swallowed, get medical help or contact a Poison Control Center right away

INACTIVE INGREDIENT

Glycerin, D-Sorbitol Solution, Carboxymethylcellulose Sodium, Hydroxyapatite, Xylitol, Stevioside, Glycyrrhiza Extract, Protease, Sodium Chloride, Camomille Extract(1), Scutellaria Root Extract, Sage Extract, Gentiana Extract, Fennel Extract , Sodium Cocoyl Glutamate, Tocopheryl Acetate, Mastic Oil, Eucalyptus Globulus Leaf Oil, L-Menthol, Peppermint Oil, Anethole, Carvone, Chamaecyparis Obtusa Oil, Potassium nitrate, Purified Water